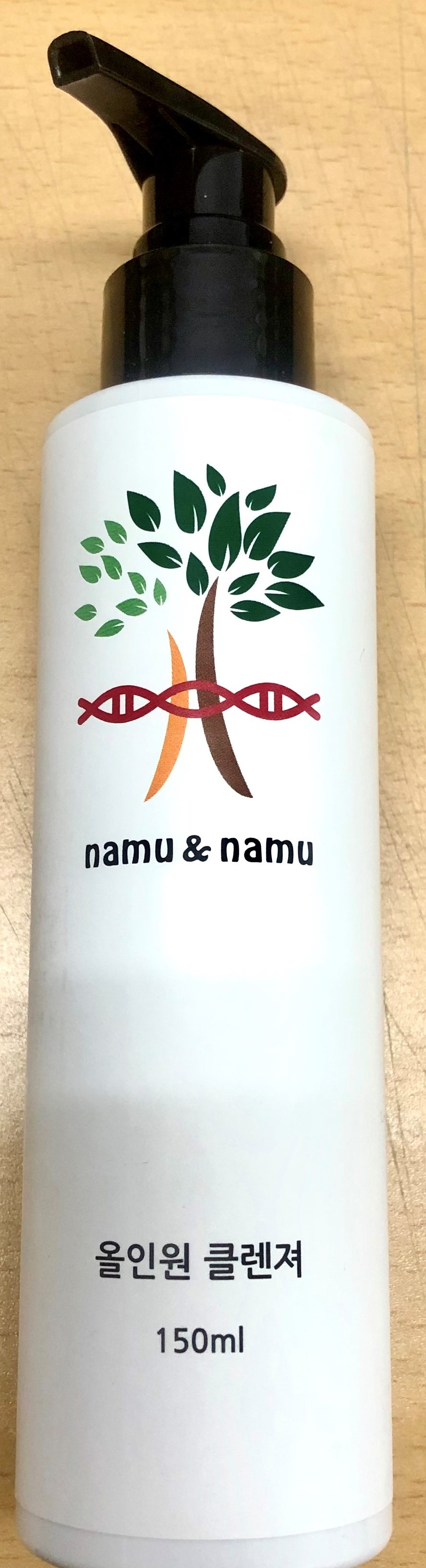 DRUG LABEL: all-in-one cleanser
NDC: 80453-100 | Form: GEL
Manufacturer: O2 Clean
Category: otc | Type: HUMAN OTC DRUG LABEL
Date: 20201013

ACTIVE INGREDIENTS: GLYCERIN 2 g/100 mL
INACTIVE INGREDIENTS: WATER; PANTHENOL; MORUS ALBA STEM; DISODIUM LAURETH SULFOSUCCINATE; GLYCYRRHIZA GLABRA

ACTIVE INGREDIENT

Glycerin

INACTIVE INGREDIENT

Broussonetia Extract
Morus Alba Stem Extract
Disodium Laureth Sulfosuccinate
Glycyrrhiza Glabra (Licorice) Root Extract
Coco-Clucoside
Sodium Cocoyl Apple Amino Acids
Houttuynia Cordata Extract
Taraxacum Officinale (Dandelion) Leaf Extract
Phellodendron Amurense Bark Extract
Broussonetia Extract
Saururus Chinensis Extract
Eucommia Ulmoides Extract
Torilis Japonica Extract
Camellia Sinensis Leaf Extract
Olea Europaea (Olive) Fruit Oil
Paeonia Suffruticosa Root Extract
Scutellaria Baicalensis Root Extract
Panthenol
Xanthan Gum
Argania Spinosa Kernel Oil
Helianthus Annuus (Sunflower) Seed Oil
Vitis Vinifera (Grape) Seed Oil
Citric Acid
Butylene Glycol
Ethylhexylglycerin
Aroma
Silk Amino Acids
Glyceryl Caprylate
Salvia Sclarea (Clary) Oil
Melaleuca Alternifolia (Tea Tree) Leaf Oil
Cymbopogon Flexuosus Oil
Lavandula Angustifolia (Lavender) Oil
Propolis Extract

PURPOSE

Skin protectant

WARNINGS

Warnings: 1. Stop using the product and consult with your general practitioner for advice if any of the following signs or symptoms appear; rash, swelling, itching and irritation during its use 2. Do not use the product for any other purpose than vaginal cleaning. Do not use this product in eyes, nose, ears and anus. 3. In case of contacting with the cleansing gel in the eyes, immediately rinse with clean water. 4. This product is single-use disposable vaginal cleanser. Please do not reuse. 5. Consult with your general practitioner for advice if you wish to use this product during pregnancy. 6. This product does not provide contraception effects. Be aware that the contraception effects may decrease if you use this product after using spermicides like vaginal contraceptive film. 7. Do not use if the individual package or any part of the applicator has been broken or damaged.

KEEP OUT OF REACH OF CHILDREN

INDICATIONS & USAGE

After pumping in an appropriate amount, lather enough and rinse thoroughly with water.

DOSAGE & ADMINISTRATION

For external use only